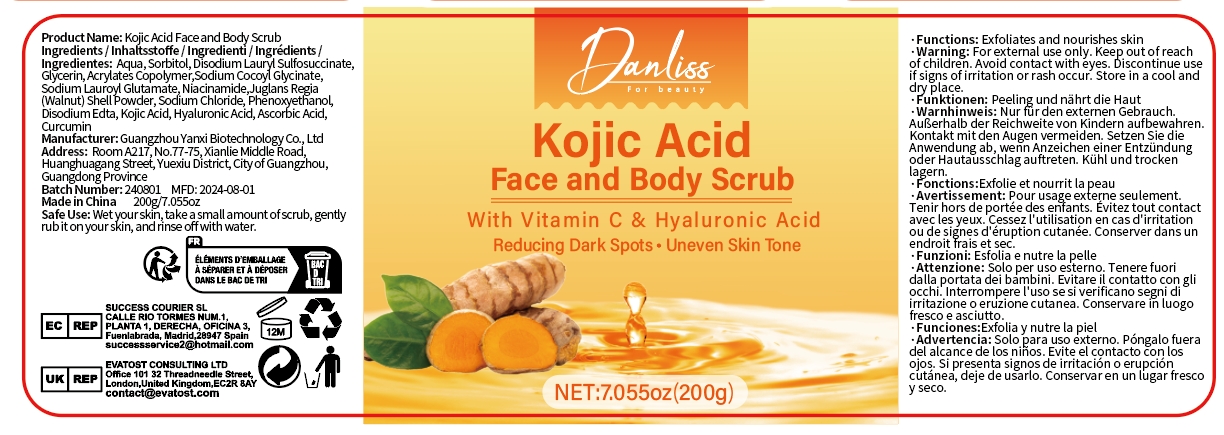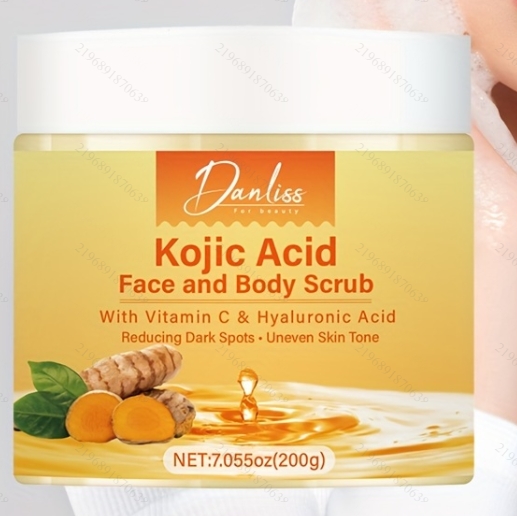 DRUG LABEL: Kojic Acid Face and Body Scrub
NDC: 84025-226 | Form: CREAM
Manufacturer: Guangzhou Yanxi Biotechnology Co., Ltd
Category: otc | Type: HUMAN OTC DRUG LABEL
Date: 20241021

ACTIVE INGREDIENTS: GLYCERIN 3 mg/100 mL; SORBITOL 5 mg/100 mL
INACTIVE INGREDIENTS: WATER

DOSAGE AND ADMINISTRATION

Wet your skin,take a small amount of scrub, gently rub it on your skin, and rinse off with water.

WARNINGS

keep out of children

INACTIVE INGREDIENT

Aqua

INDICATIONS AND USAGE

for daily body care

keep out of children

PURPOSE

By exfoliating the outer layer of the skin and promoting cell turnover, kojic acid can contribute to a smoother and more youthful-looking complexion. It may also have mild anti-aging effects by reducing the appearance of fine lines and wrinkles.